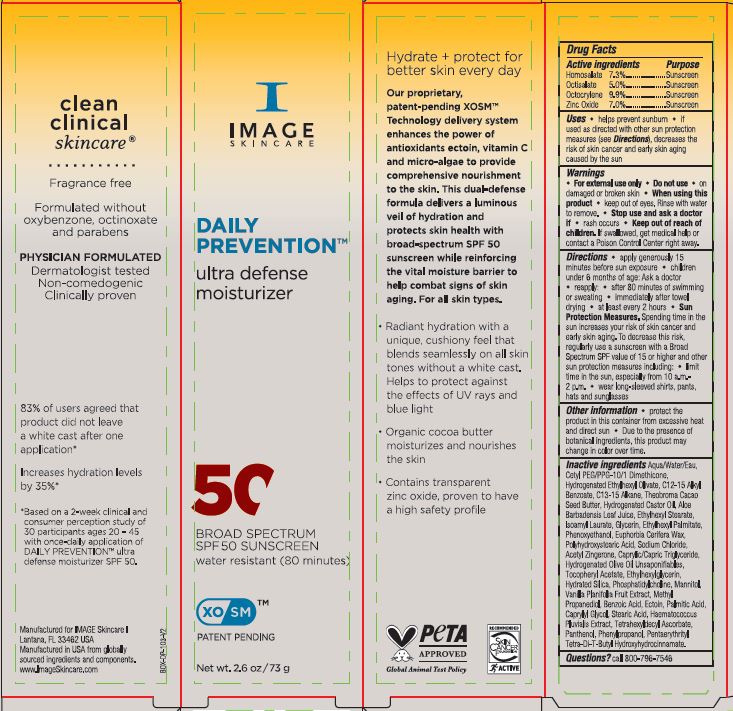 DRUG LABEL: Daily Prevention Ultra Defense Moisturizer SPF 50
NDC: 62742-4255 | Form: CREAM
Manufacturer: Allure Labs
Category: otc | Type: HUMAN OTC DRUG LABEL
Date: 20240319

ACTIVE INGREDIENTS: OCTISALATE 5 g/100 g; OCTOCRYLENE 9.9 g/100 g; ZINC OXIDE 7 g/100 g; HOMOSALATE 7.3 g/100 g
INACTIVE INGREDIENTS: CETYL PEG/PPG-10/1 DIMETHICONE (HLB 4); C13-15 ALKANE; GLYCERIN; ETHYLHEXYL PALMITATE; SODIUM CHLORIDE; TETRAHEXYLDECYL ASCORBATE; METHYLPROPANEDIOL; BENZOIC ACID; ECTOINE; ALOE VERA LEAF; ALKYL (C12-15) BENZOATE; PHENYLPROPANOL; VANILLA; HYDRATED SILICA; PHOSPHATIDYLCHOLINE TRANSLOCATOR ABCB4; MANNITOL; WATER; HYDROGENATED CASTOR OIL; ACETYL ZINGERONE; STEARIC ACID; COCOA BUTTER; ETHYLHEXYL STEARATE; ISOAMYL LAURATE; PHENOXYETHANOL; CANDELILLA WAX; POLYHYDROXYSTEARIC ACID (2300 MW); HYDROGENATED OLIVE OIL UNSAPONIFIABLES; CAPRYLYL GLYCOL; PANTHENOL; .ALPHA.-TOCOPHEROL ACETATE; ETHYLHEXYLGLYCERIN; HYDROGENATED ETHYLHEXYL OLIVATE; MEDIUM-CHAIN TRIGLYCERIDES; HAEMATOCOCCUS PLUVIALIS; PENTAERYTHRITOL TETRAKIS(3-(3,5-DI-TERT-BUTYL-4-HYDROXYPHENYL)PROPIONATE); PALMITIC ACID

Drug Facts

Active ingredients

Homosalate 7.3%

Octisalate 5.0%

Octocrylene 9.9%

Zinc Oxide 7.0%

Purpose; Sunscreen

INDICATIONS AND USAGE

Uses • helps prevent sunburn • if used as directed with other sun protection measures (see Directions), decreases the risk of skin cancer and early skin aging caused by the sun.

Warnings • For external use only

Do not use • on damaged or broken skin

When using this product • keep out of eyes. Rinse with water to remove.

Stop use and ask a doctor if • rash occurs

Keep out of reach of children. If swallowed, get medical help or contact a Poison Control Center right away.

DOSAGE AND ADMINISTRATION

Directions • apply generously 15 minutes before sun exposure • children under 6 months of age: Ask a doctor • reapply: • after 80 minutes of swimming or sweating • immediately after towel drying • at least every 2 hours • Sun Protection Measures. Spending time in the sun increases your risk of skin cancer and early skin aging. To decrease this risk, regularly use a sunscreen with a Broad Spectrum SPF value of 15 or higher and other sun protection measures including: • limit time in the sun, especially from 10 a.m.-2 p.m. • wear long-sleeved shirts, pants, hats and sunglasses

Other information • protect the product in this container from excessive heat and direct sun • Due to the presence of botanical ingredients, this product may change in color over time.

INACTIVE INGREDIENT

Inactive ingredients : Aqua/Water/Eau, Cetyl PEG/PPG-10/1 Dimethicone, Hydrogenated Ethylhexyl Olivete, C12-15 Alkyl Benzoate, C13-15 Alkane, Theobroma Cacao Seed Butter, Hydrogenated Castor Oil, Aloe Barbadensis Leaf Juice, Ethylhexyl Stearate, Isoamyl Laurate, Glycerin, Ethylhexyl Palmitate, Phenoxyethanol, Euphorbia Cerifera Wax, Polyhydroxystearic Acid, Sodium Chloride, Acetyl Zingerone, Caprylic/Capric Triglyceride, Hydrogenated Olive Oil Unsaponifiables, Tocopheryl Acetate, Ethylhexylglycerin, Hydrated Silica, Phosphatidylcholine, Mannitol, Vanilla Planifolia Fruit Extract, Methyl Propanediol, Benzoic Acid, Ectoin, Palmitic Acid, Caprylyl Glycol, Stearic Acid, Haematococcus Pluvialis Extract, Tetrahexyldecyl Ascorbate, Panthenol, Phenylpropanol, Pentaerythrityl Tetra-Di-T-Butyl Hydroxydrocinnamate.